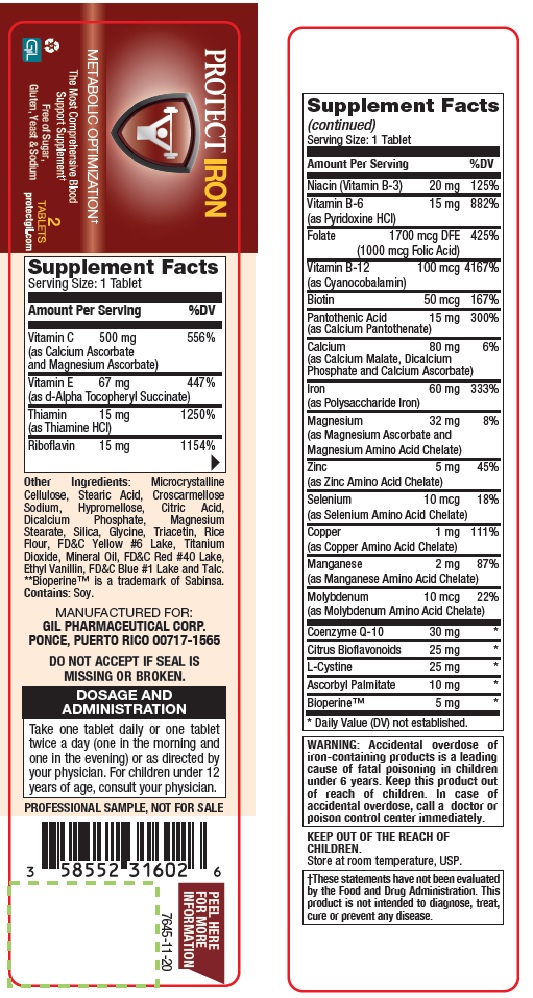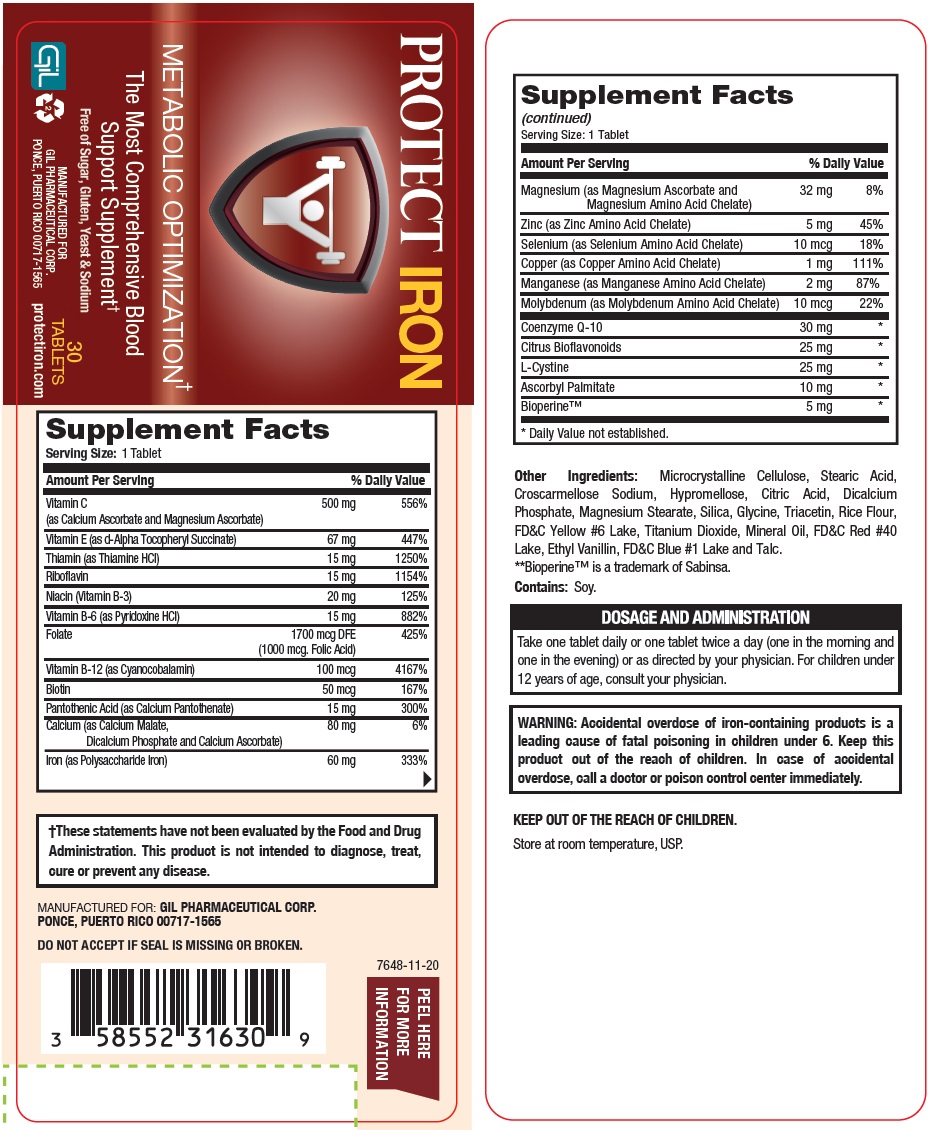 DRUG LABEL: PROTECT IRON
NDC: 58552-316 | Form: TABLET
Manufacturer: GIL PHARMACEUTICAL CORP.
Category: other | Type: DIETARY SUPPLEMENT
Date: 20221105

ACTIVE INGREDIENTS: ASCORBIC ACID 500 mg/1 1; .ALPHA.-TOCOPHEROL 67 mg/1 1; THIAMINE 15 mg/1 1; RIBOFLAVIN 15 mg/1 1; NIACIN 20 mg/1 1; PYRIDOXINE 15 mg/1 1; FOLIC ACID 1.7 mg/1 1; CYANOCOBALAMIN 0.1 mg/1 1; BIOTIN 0.05 mg/1 1; PANTOTHENIC ACID 15 mg/1 1; CALCIUM 80 mg/1 1; IRON 60 mg/1 1; MAGNESIUM 32 mg/1 1; ZINC 5 mg/1 1; SELENIUM 0.01 mg/1 1; COPPER 1 mg/1 1; MANGANESE 2 mg/1 1; MOLYBDENUM 0.01 mg/1 1; UBIDECARENONE 30 mg/1 1; CITRUS BIOFLAVONOIDS 25 mg/1 1; CYSTINE 25 mg/1 1; ASCORBYL PALMITATE 10 mg/1 1; PIPERINE 5 mg/1 1
INACTIVE INGREDIENTS: MICROCRYSTALLINE CELLULOSE; STEARIC ACID; CROSCARMELLOSE SODIUM; HYPROMELLOSE, UNSPECIFIED; CITRIC ACID MONOHYDRATE; ANHYDROUS DIBASIC CALCIUM PHOSPHATE; MAGNESIUM STEARATE; SILICON DIOXIDE; GLYCINE; TRIACETIN; BROWN RICE; FD&C YELLOW NO. 6; TITANIUM DIOXIDE; MINERAL OIL; FD&C RED NO. 40; ETHYL VANILLIN; FD&C BLUE NO. 1 ALUMINUM LAKE; TALC

PROTECT IRON
METABOLIC OPTIMIZATION†
The Most Comprehensive Blood Support Supplement
Free of Sugar, Gluten, Yeast & Sodium

STATEMENT OF IDENTITY

Supplement Facts Serving Size: 1 Tablet
Amount Per Serving |  | % DailyValue
Vitamin C; (as Calcium Ascorbate and Magnesium Ascorbate) | 500 mg | 556%
Vitamin E (as d-Alpha Tocopheryl Succinate) | 67 mg | 447%
Thiamin (as Thiamine HCl) | 15 mg | 1250%
Riboflavin | 15 mg | 1154%
Niacin (Vitamin B-3) | 20 mg | 125%
Vitamin B-6 (as Pyridoxine HCl) | 15 mg | 882%
Folate | 1700 mcg DFE; (1000 mcg Folic Acid) | 425%
Vitamin B-12 (as Cyanocobalamin) | 100 mcg | 4167%
Biotin | 50 mcg | 167%
Pantothenic Acid (as Calcium Pantothenate) | 15 mg | 300%
Calcium (as Calcium Malate,; Dicalcium Phosphate and Calcium Ascorbate) | 80 mg | 6%
Iron (as Polysaccharide Iron) | 60 mg | 333%
Magnesium (as Magnesium Ascorbate and; Magnesium Amino Acid Chelate) | 32 mg | 8%
Zinc (as Zinc Amino Acid Chelate) | 5 mg | 45%
Selenium (as Selenium Amino Acid Chelate) | 10 mcg | 18%
Copper (as Copper Amino Acid Chelate) | 1 mg | 111%
Manganese (as Manganese Amino Acid Chelate) | 2 mg | 87%
Molybdenum (as Molybdenum Amino Acid Chelate) | 10 mcg | 22%
Coenzyme Q-10 | 30 mg | *
Citrus Bioflavonoids | 25 mg | *
L-Cystine | 25 mg | *
Ascorbyl Palmitate | 10 mg | *
Bioperine™ | 5 mg | *
*Daily Value (DV) not established.

WARNINGS

WARNING: Accidental overdose of iron-containing products is a leading cause of fatal poisoning in children under 6. Keep this product out of the reach of children. In case of accidental overdose, call a doctor or poison control center immediately.

STATEMENT OF IDENTITY

KEEP OUT OF THE REACH OF CHILDREN.

Store at room temperature, USP.

SAFE HANDLING WARNING

†These statements have not been evaluated by the Food and Drug Administration. This product is not intended to diagnose, treat, cure or prevent any disease.

HEALTH CLAIM

Other Ingredients: Microcrystalline Cellulose, Stearic Acid, Croscarmellose Sodium, Hypromellose, Citric Acid, Dicalcium Phosphate, Magnesium Stearate, Silica, Glycine, Triacetin, Rice Flour, FD&C Yellow #6 Lake, Titanium Dioxide, Mineral Oil, FD&C Red #40 Lake, Ethyl Vanillin, FD&C Blue #1 Lake and Talc.

**Bioperine™ is a trademark of Sabinsa.
Contains: Soy.

DOSAGE AND ADMINISTRATION

Take one tablet daily or one tablet twice a day (one in the morning and one in the evening) or as directed by your physician. For children under 12 years of age, consult your physician.

PRECAUTIONS

MANUFACTURED FOR:
GIL PHARMACEUTICAL CORP.

PONCE, PUERTO RICO 00717-1565

DO NOT ACCEPT IF SEAL IS MISSING OR BROKEN.
PROFESSIONAL SAMPLE, NOT FOR SALE

PAKAGE LABEL.PRINCIPAL DISPLAY PANEL

Protect Iron Metabolic Optimization NDC-58552-316-30 - 30s Label

Protect Iron Metabolic Optimization -NDC-58552-316-02-2s Label